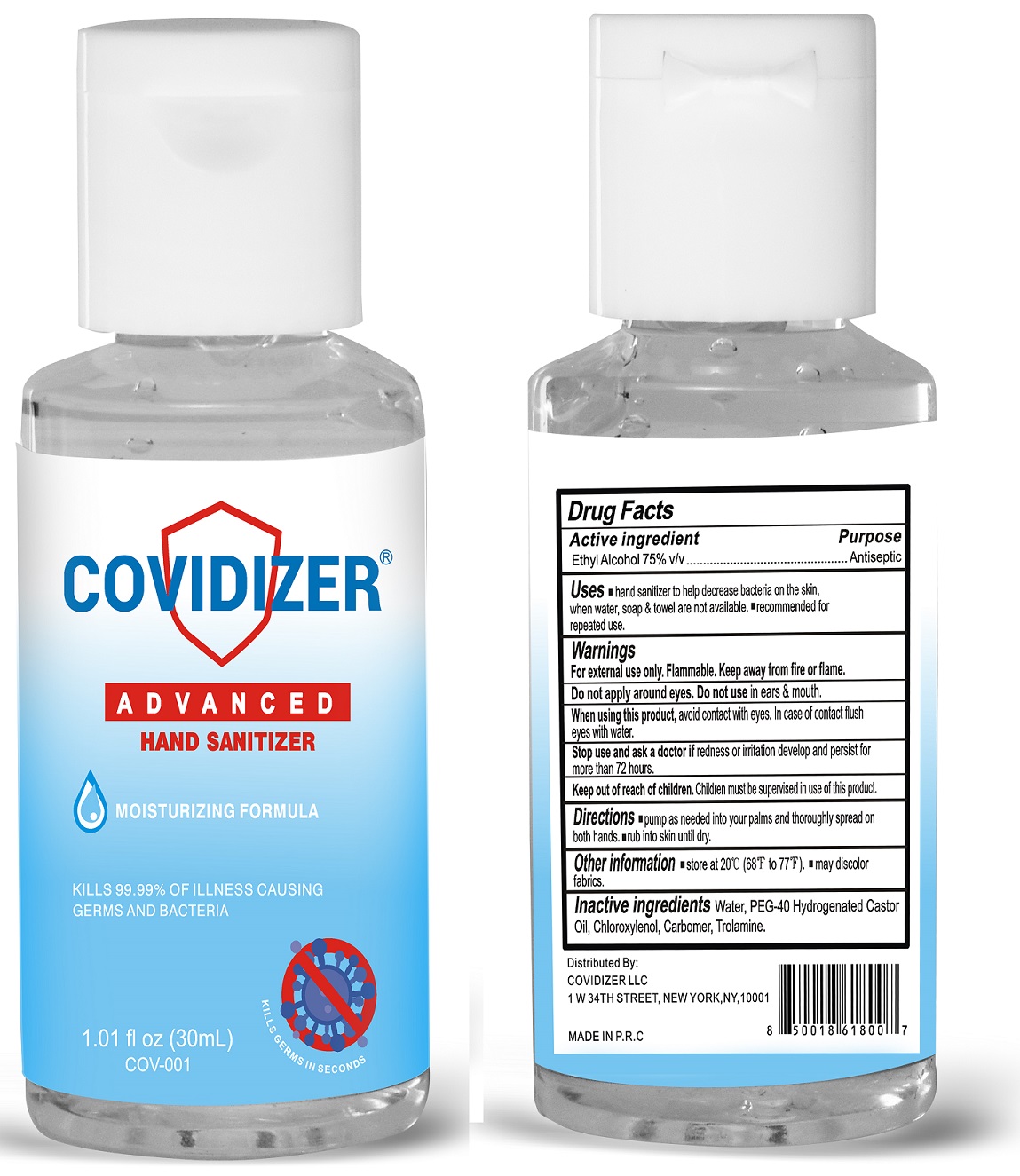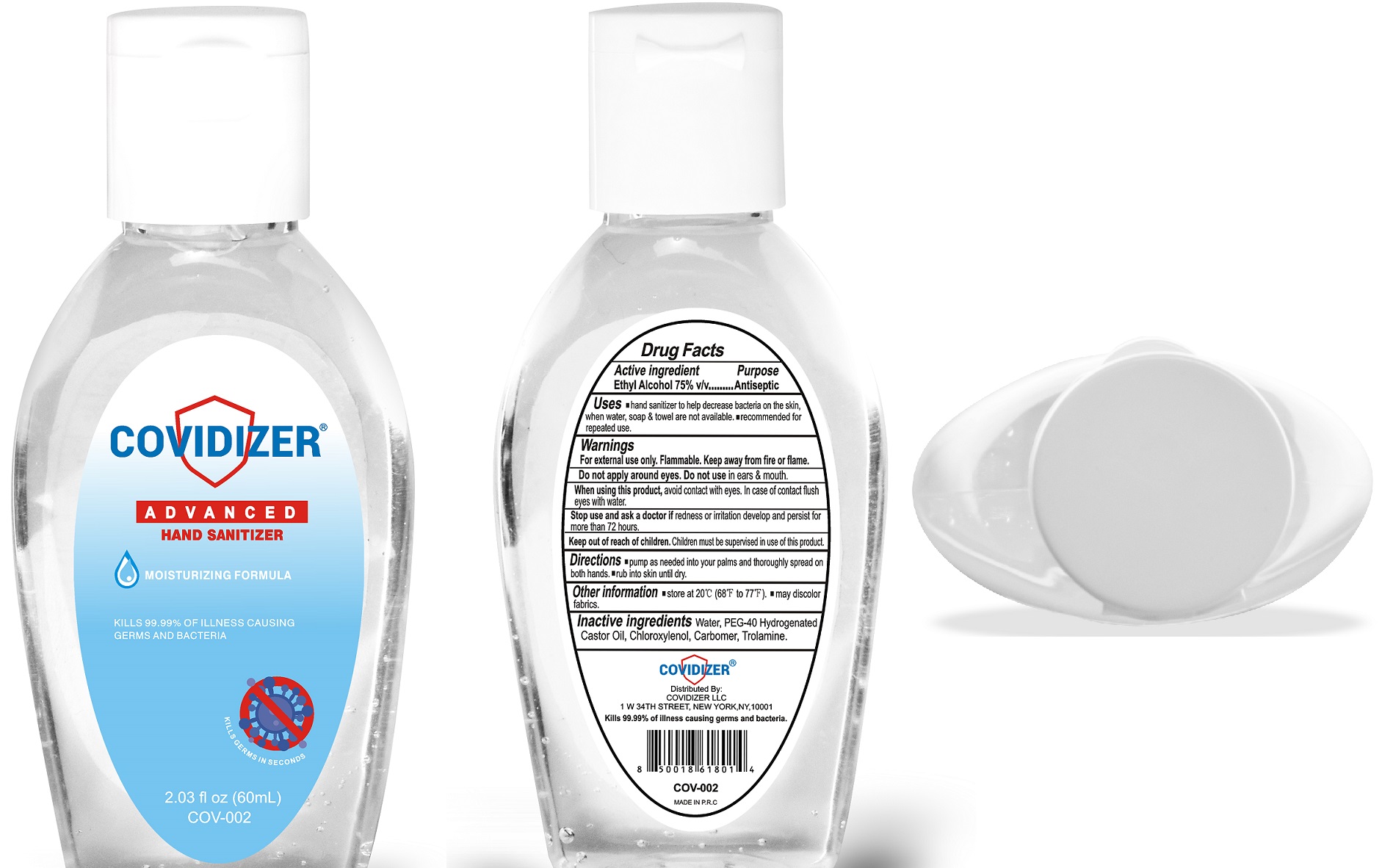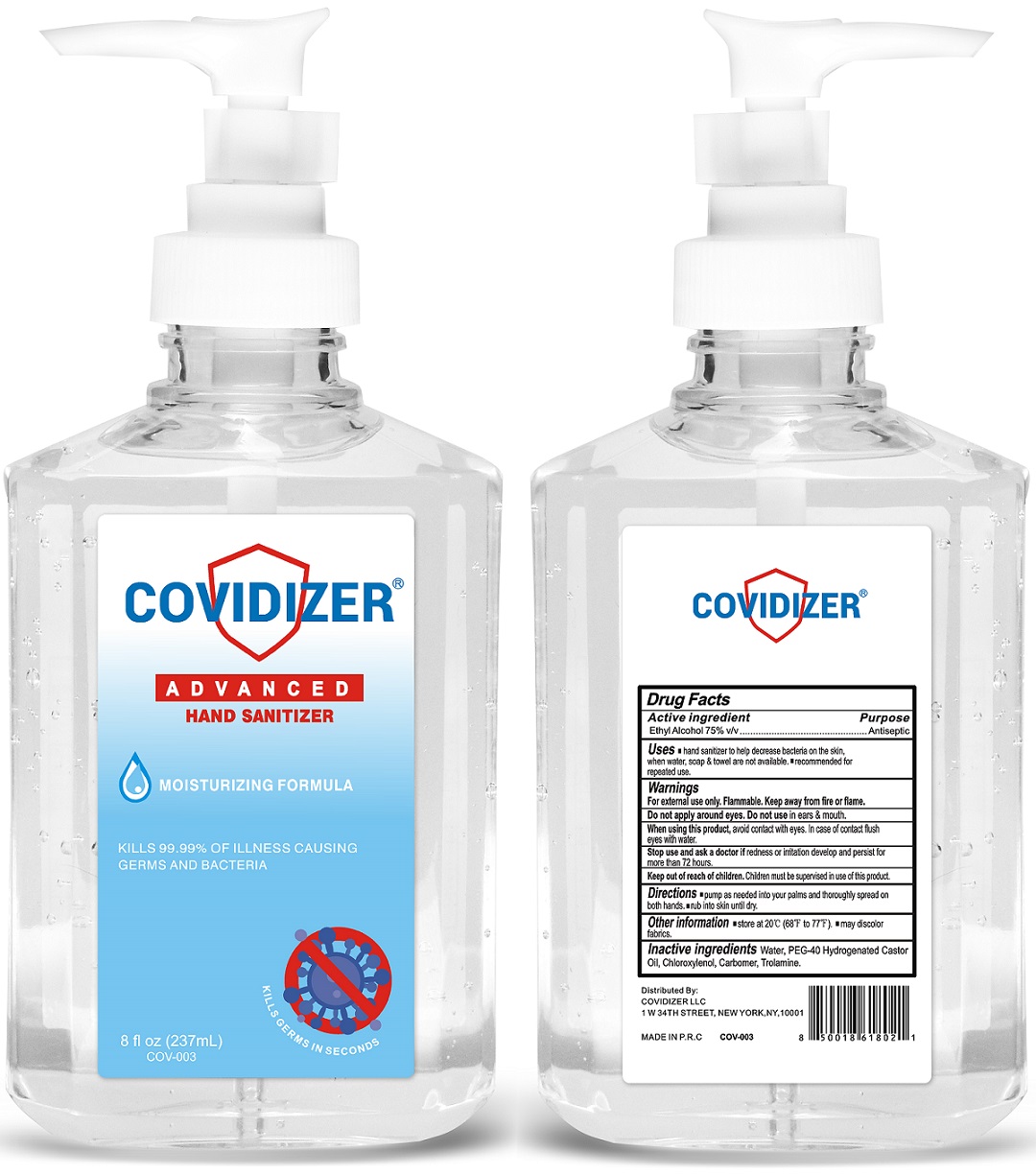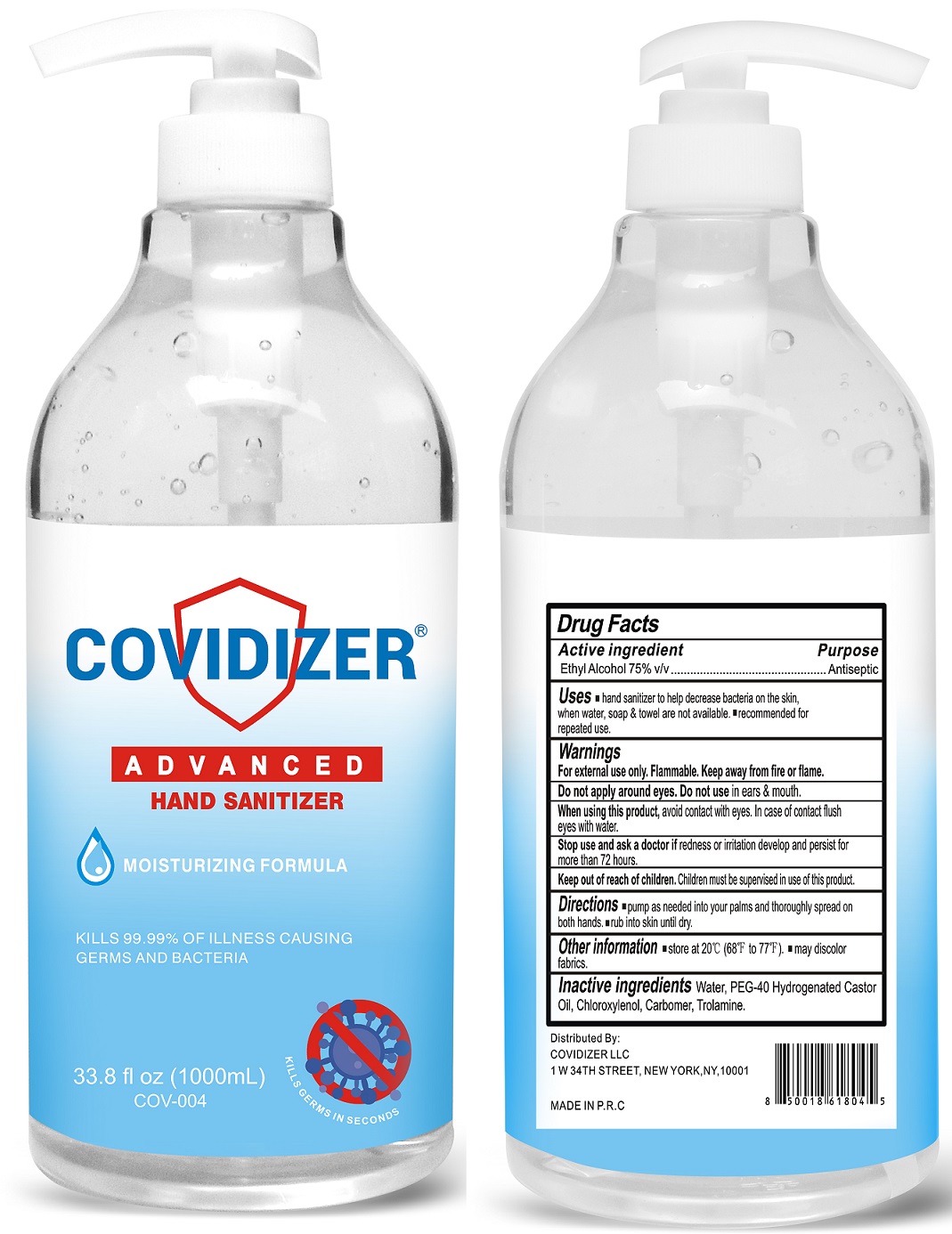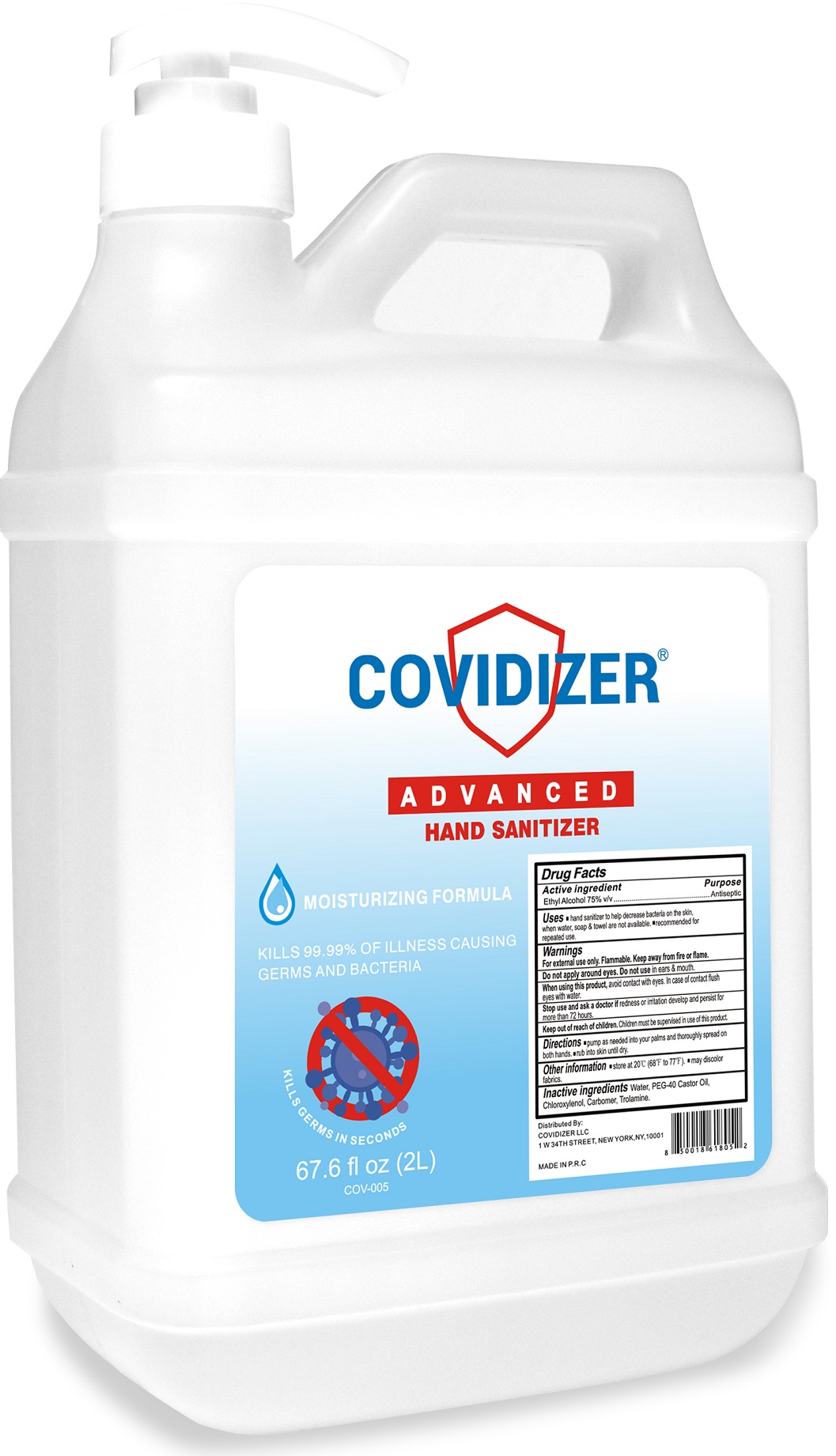 DRUG LABEL: Covidizer Hand Sanitizer
NDC: 78715-000 | Form: GEL
Manufacturer: Covidizer, LLC
Category: otc | Type: HUMAN OTC DRUG LABEL
Date: 20201208

ACTIVE INGREDIENTS: ALCOHOL 0.75 mL/1 mL
INACTIVE INGREDIENTS: WATER; POLYOXYL 40 HYDROGENATED CASTOR OIL; CHLOROXYLENOL; CARBOMER HOMOPOLYMER, UNSPECIFIED TYPE; TROLAMINE

Covidizer Hand Sanitizer

Active ingredient

Ethyl Alcohol 75% v/v

Purpose

Antiseptic

Uses

- hand sanitizer to help decrease bacteria on the skin, when water, soap & towel are not availble.
- recommended for repeated use.

Warnings

For external use only. Flammable. Keep away from fire or flame.

Do not apply around eyes.

Do not use

in ears & mouth.

When using this product,

avoid contact with eyes. In case of contact flush eyes with water.

Stop use and ask a doctor if

redness or irritation develop and persist for more than 72 hours.

Keep out of reach of children.

Children must be supervised in use of this product.

Directions

- pump as needed into your palms and thoroughly spread on both hands.
- rub into skin until dry.

Other information

- store at 20°C (68°F to 77°F).
- may discolor fabrics.

Inactive ingredients

Water, PEG-40 Hydrogenated Castor Oil, Chloroxylenol, Carbomer, Trolamine.